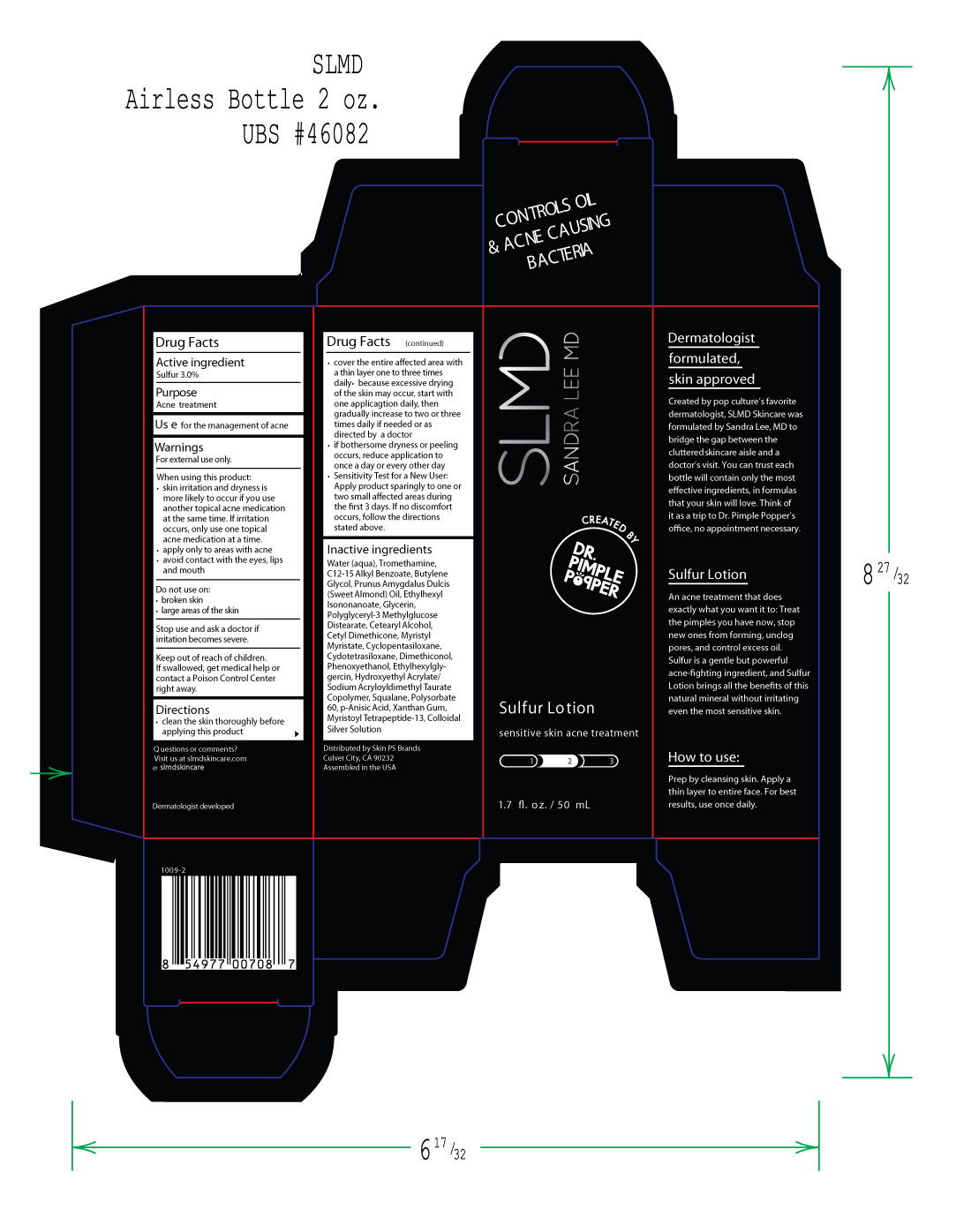 DRUG LABEL: SLMD Silver Sulfur Acne Cream
NDC: 59958-407 | Form: CREAM
Manufacturer: Owen Biosciences Inc.
Category: otc | Type: HUMAN OTC DRUG LABEL
Date: 20250113

ACTIVE INGREDIENTS: SULFUR 3 g/100 g
INACTIVE INGREDIENTS: WATER 71.69 g/100 g; BUTYLENE GLYCOL 3 g/100 g; ALMOND OIL 3 g/100 g

SLMD Silver Sulfur Acne Cream -407

Active Ingredient

Sulfur 3.0%

Purpose

Acne Treatment

Use

Use for the management of acne

Warnings For external use only.

When using this product:
• skin irritation and dryness is
more likely to occur if you use
another topical acne medication
at the same time. If irritation
occurs, only use one topical
acne medication at a time.
•apply only to areas with acne
• avoid contact with the eyes, lips, and mouth

Do not use on:
• broken skin
• large areas of the skin

Stop use and ask a doctor if
irriatation becomes servere.

Keep out of reach of children.
If swallowed, get medical help or
contact a Poison Control Center
right away

Directions

• clean the skin thoroughly before
applying this product
• cover the entire affected area with
a thin layer one to three times
daily • because excessive drying
of the skin may occur, start with
one applicagtion daily, then
gradually increase to two or three
times daily if needed or as
directed by a doctor
• if bothersome dryness or peeling
occurs, reduce application to
once a day or every other day
• Sensitivity Test for a New User:
Apply product sparingly to one or
two small affected areas during
the first 3 days. If no discomfort
occurs, follow the directions
stated above.

INACTIVE INGREDIENT

Water (aqua), Tromethamine,
C12-15 Alkyl Benzoate, Butylene
Glycol, Prunus Amygdalus Dulcis
(Sweet Almond) Oil, Ethylhexyl
Isononanoate, Glycerin,
Polyglyceryl-3 Methylglucose
Distearate, Cetearyl Alcohol,
Cetyl Dimethicone, Myristyl
Myristate, Cyclopentasiloxane,
Cydotetrasiloxane, Dimethiconol,
Phenoxyethanol, Ethylhexylgly-
gercin, Hydroxyethyl Acrylate/
Sodium Acryloyldimethyl Taurate
Copolymer, Squalane, Polysorbate
60, p-Anisic Acid, Xanthan Gum,
Myristoyl Tetrapeptide-13, Colloidal
Silver Solution

Keep out of reach of children.

If swallowed, get medical help or
contact a Poison Control Center
right away

Sulfur Carton.jpg